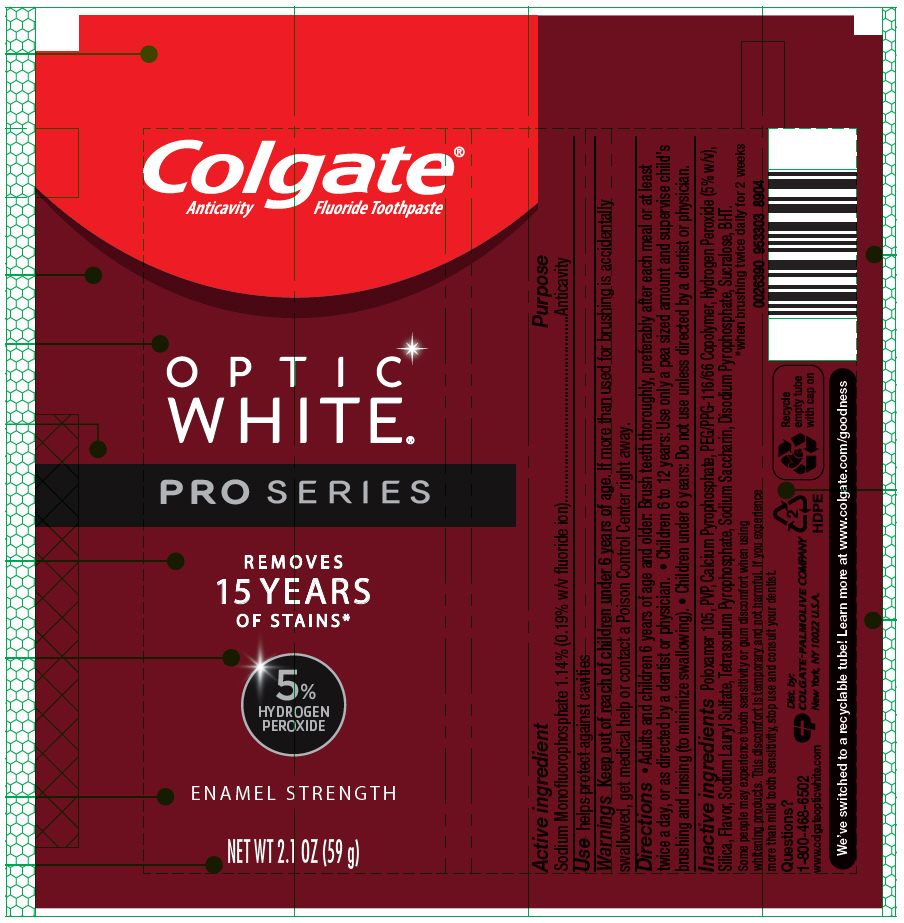 DRUG LABEL: Colgate Optic White ProSeries Enamel Strenght
NDC: 35000-748 | Form: PASTE, DENTIFRICE
Manufacturer: COLGATE PALMOLIVE COMPANY
Category: otc | Type: HUMAN OTC DRUG LABEL
Date: 20191031

ACTIVE INGREDIENTS: SODIUM MONOFLUOROPHOSPHATE 1.5 mg/1 g
INACTIVE INGREDIENTS: POLOXAMER 105 446 mg/1 g; CROSPOVIDONE, UNSPECIFIED; CALCIUM PYROPHOSPHATE; PEG/PPG-116/66 COPOLYMER; HYDROGEN PEROXIDE; SILICON DIOXIDE; SODIUM LAURYL SULFATE; SODIUM PYROPHOSPHATE; SACCHARIN SODIUM; SODIUM ACID PYROPHOSPHATE; SUCRALOSE; BUTYLATED HYDROXYTOLUENE

Colgate® Optic White® ProSeries Enamel Strength

Active ingredient

Sodium Monofluorophosphate 1.14% (0.19% w/v fluoride ion)

Purpose

Anticavity

Use

helps protect against cavities

Warnings

Keep out of reach of children under 6 years of age. If more than used for brushing is accidentally swallowed, get medical help or contact a Poison Control Center right away.

Directions

- Adults and children 6 years of age and older: Brush teeth thoroughly, preferably after each meal or at least twice a day, or as directed by a dentist or physician.
- Children 6 to 12 years: Use only a pea sized amount and supervise child's brushing and rinsing (to minimize swallowing).
- Children under 6 years: Do not use unless directed by a dentist or physician.

Inactive ingredients

Poloxamer 105, PVP, Calcium Pyrophosphate, PEG/PPG-116/66 Copolymer, Hydrogen Peroxide (5% w/v), Silica, Flavor, Sodium Lauryl Sulfate, Tetrasodium Pyrophosphate, Sodium Saccharin, Disodium Pyrophosphate, Sucralose, BHT.

Questions?

1-800-468-6502

Dist. by:
COLGATE-PALMOLIVE COMPANY
New York, NY 10022 U.S.A.

PRINCIPAL DISPLAY PANEL - 59 g Tube Label

Colgate®
Anticavity Fluoride Toothpaste

OPTIC
WHITE®

PRO SERIES

REMOVES
15 YEARS
OF STAINS*

5%
HYDROGEN
PEROXIDE

ENAMEL STRENGTH

NET WT 2.1 OZ (59 g)